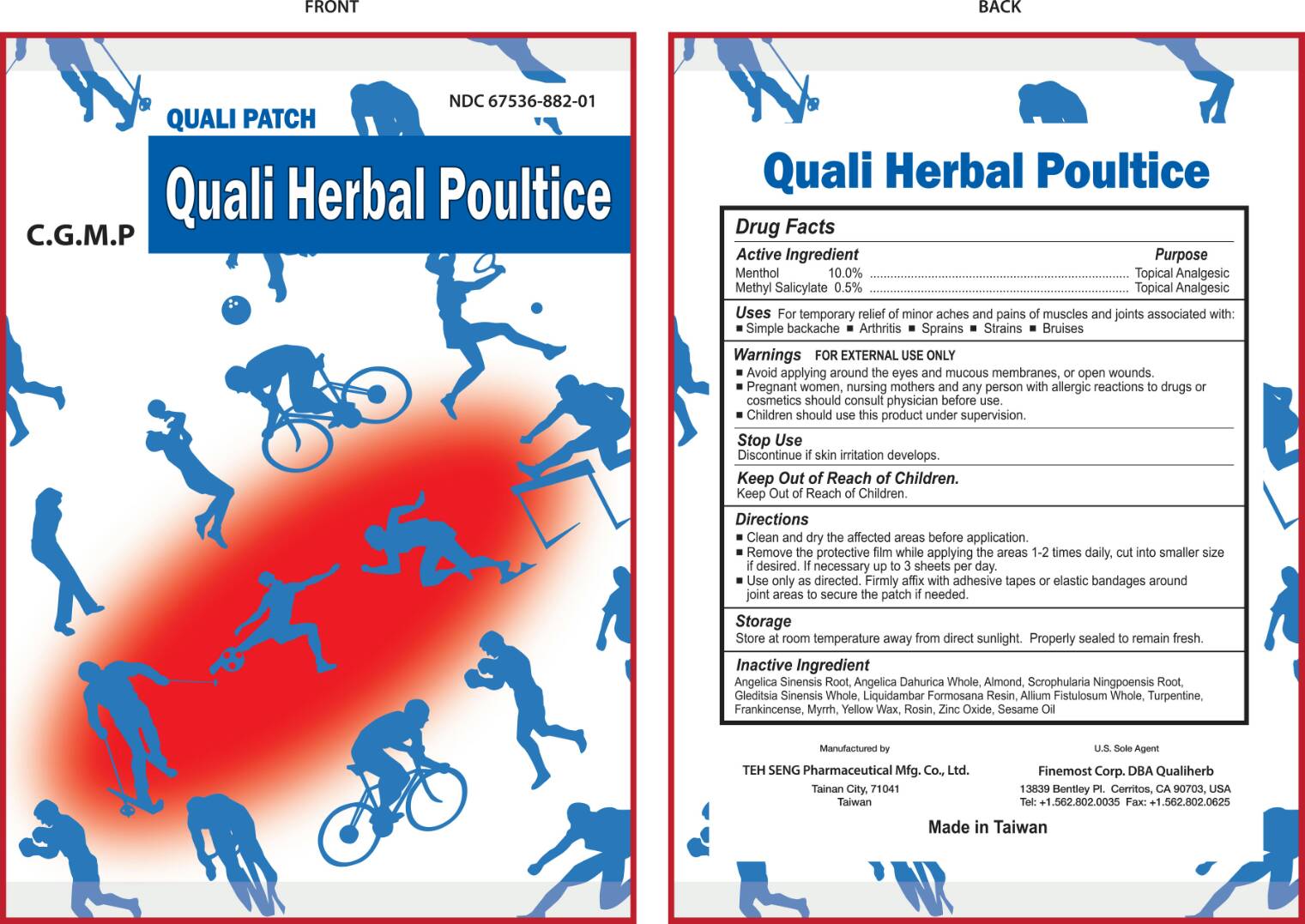 DRUG LABEL: QUALI HERBAL
NDC: 67536-882 | Form: PATCH
Manufacturer: Teh Seng Pharmaceutical Mfg. Co., Ltd
Category: otc | Type: HUMAN OTC DRUG LABEL
Date: 20161012

ACTIVE INGREDIENTS: MENTHOL 10 g/100 g; METHYL SALICYLATE 0.5 g/100 g
INACTIVE INGREDIENTS: ANGELICA SINENSIS ROOT; ANGELICA DAHURICA WHOLE; ALMOND; SCROPHULARIA NINGPOENSIS ROOT; GLEDITSIA SINENSIS WHOLE; LIQUIDAMBAR FORMOSANA RESIN; ALLIUM FISTULOSUM WHOLE; TURPENTINE; FRANKINCENSE; MYRRH; YELLOW WAX; ROSIN; ZINC OXIDE; SESAME OIL

Teh Seng Pharmaceutical Mfg. Co., Ltd

ACTIVE INGREDIENTS

Menthol 10%

Methyl Salicylate 0.5%

Purpose

Menthol Topical Analgesic

Methyl Salicylate Topical Analgesic

Uses

For temporary relief of minor aches and pains of muscles and joints associated with:

Simple backache
Arthritis
Sprains
Strains
Bruises

Warnings

1. For external use only. Avoid applying around the eyes and mucous membranes, or open wounds.
2. Pregnant women, nursing mothers and any person with allergic reactions to drugs or cosmetics should consult physician before use. Children should use this product under supervision.

Stop Use

Discontinue if skin irritation develops.

Keep Out Of Reach of Children.

Directions

1. Clean and dry the affected areas before application.
2. Remove the protective film while applying the areas 1-2 times daily, cut into smaller size if desired. If necessary up to 3 sheets per day.
3. Use only as directed. Firmly affix with adhesive tapes or elastic bandages around joint areas to secure the patch if needed.

Storage

Store at room temperature away from direct sunlight. Properly sealed to remain fresh.

Inactive Ingredients

ANGELICA SINENSIS ROOT, ANGELICA DAHURICA WHOLE, ALMOND, SCROPHULARIA NINGPOENSIS ROOT, GLEDITSIA SINENSIS WHOLE, LIQUIDAMBAR FORMOSANA RESIN, ALLIUM FISTULOSUM WHOLE, TURPENTINE, FRANKINCENSE, MYRRH, YELLOW WAX, ROSIN, ZINC OXIDE, SESAME OIL

U.S. Sole Agent

Finemost Corp., Qualiherb

Cerritos, Ca 90703

Tel: (562)802-0035

Fax: (562)802-0625

Made in Taiwan